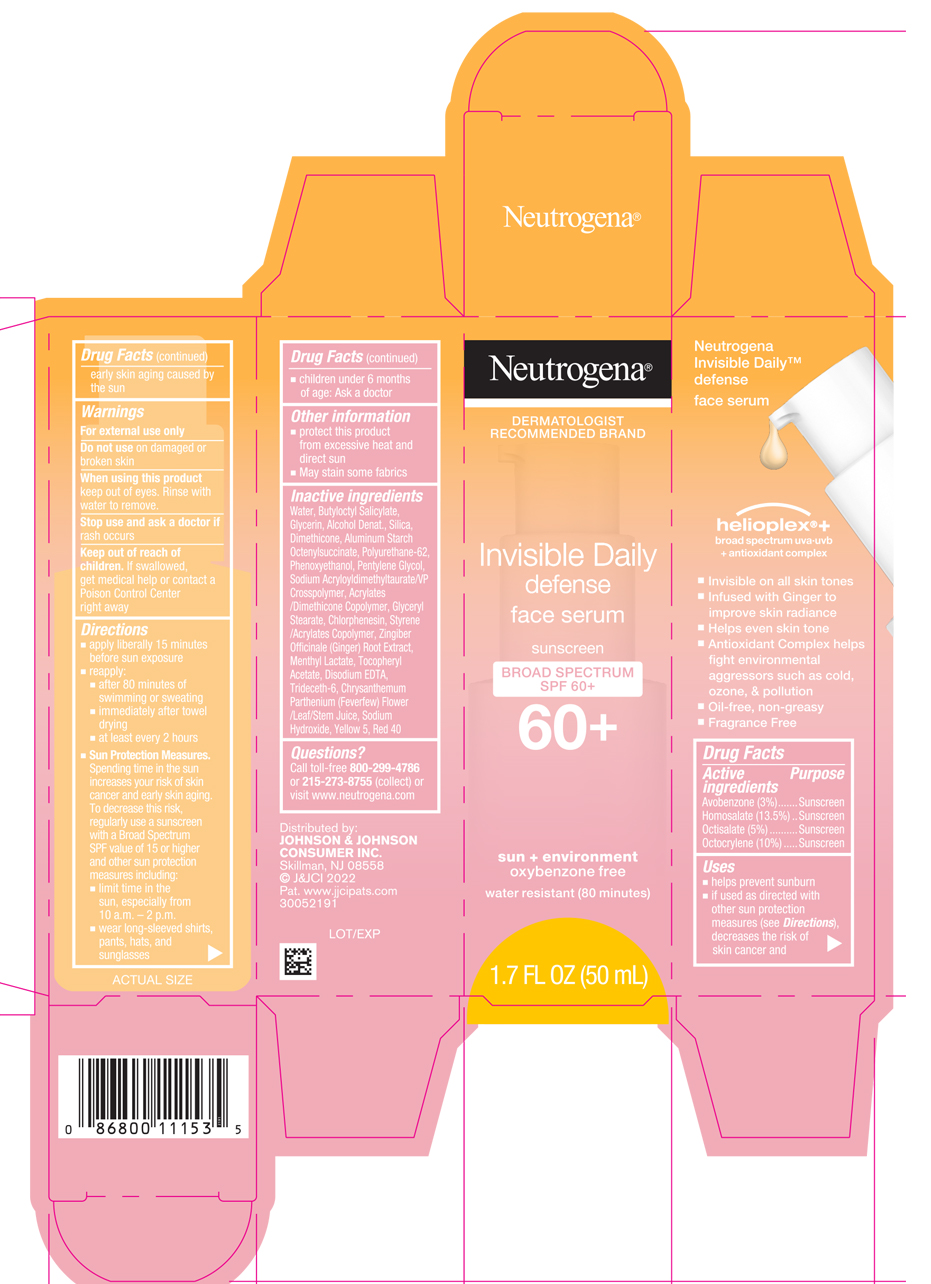 DRUG LABEL: Neutrogena Invisible Daily Defense Face Serum Sunscreen Broad Spectrum SPF 60 Plus
NDC: 69968-0681 | Form: LOTION
Manufacturer: Kenvue Brands LLC
Category: otc | Type: HUMAN OTC DRUG LABEL
Date: 20260113

ACTIVE INGREDIENTS: AVOBENZONE 30 mg/1 mL; HOMOSALATE 135 mg/1 mL; OCTISALATE 50 mg/1 mL; OCTOCRYLENE 100 mg/1 mL
INACTIVE INGREDIENTS: 2-ETHYLHEXYL ACRYLATE, METHACRYLATE, METHYL METHACRYLATE, OR BUTYL METHACRYLATE/HYDROXYPROPYL DIMETHICONE COPOLYMER (30000-300000 MW); WATER; BUTYLOCTYL SALICYLATE; GLYCERIN; ALCOHOL; SILICON DIOXIDE; DIMETHICONE; ALUMINUM STARCH OCTENYLSUCCINATE; PHENOXYETHANOL; PENTYLENE GLYCOL; BUTYL METHACRYLATE/METHYL METHACRYLATE/METHACRYLIC ACID/STYRENE CROSSPOLYMER; GLYCERYL MONOSTEARATE; .ALPHA.-TOCOPHEROL ACETATE; CHLORPHENESIN; GINGER; MENTHYL LACTATE, (-)-; EDETATE DISODIUM ANHYDROUS; TRIDECETH-6; FEVERFEW; SODIUM HYDROXIDE; FD&C YELLOW NO. 5; FD&C RED NO. 40; POLYURETHANE-62

Neutrogena® Invisible Daily defense face serum sunscreen BROAD SPECTUM SPF 60+

Drug Facts

ACTIVE INGREDIENT

Active ingredients | Purpose
Avobenzone 3% | Sunscreen
Homosalate 13.5% | Sunscreen
Octisalate 5% | Sunscreen
Octocrylene 10% | Sunscreen

Uses

- helps prevent sunburn
- if used as directed with other sun protection measures (see Directions), decreases the risk of skin cancer and early skin aging caused by the sun

Warnings

For external use only

Do not use on damaged or broken skin

When using this product keep out of eyes. Rinse with water to remove.

Stop use and ask a doctor if rash occurs

Keep out of reach of children. If swallowed, get medical help or contact a Poison Control Center right away

Directions

- apply liberally 15 minutes before sun exposure
- reapply:
  - after 80 minutes of swimming or sweating
  - immediately after towel drying
  - at least every 2 hours
- Sun Protection Measures. Spending time in the sun increases your risk of skin cancer and early skin aging. To decrease this risk, regularly use a sunscreen with a Broad Spectrum SPF value of 15 or higher and other sun protection measures including:
  - limit time in the sun, especially from 10 a.m. – 2 p.m.
  - wear long-sleeved shirts, pants, hats, and sunglasses
- children under 6 months of age: Ask a doctor

Other information

- protect this product from excessive heat and direct sun
- May stain some fabrics

Inactive ingredients

Water, Butyloctyl Salicylate, Glycerin, Alcohol Denat., Silica, Dimethicone, Aluminum Starch Octenylsuccinate, Polyurethane-62, Phenoxyethanol, Pentylene Glycol, Sodium Acryloyldimethyltaurate/VP Crosspolymer, Acrylates/Dimethicone Copolymer, Glyceryl Stearate, Chlorphenesin, Styrene/Acrylates Copolymer, Zingiber Officinale (Ginger) Root Extract, Menthyl Lactate, Tocopheryl Acetate, Disodium EDTA, Trideceth-6, Chrysanthemum Parthenium (Feverfew) Flower/Leaf/Stem Juice, Sodium Hydroxide, Yellow 5, Red 40

Questions?

Call toll-free 800-299-4786 or 215-273-8755 (collect) or visit www.neutrogena.com

Distributed by:
JOHNSON & JOHNSON
CONSUMER INC.
Skillman, NJ 08558

PRINCIPAL DISPLAY PANEL - 50 mL Bottle Carton

Neutrogena®
DERMATOLOGIST
RECOMMENDED BRAND

Invisible Daily
defense

face serum
sunscreen

BROAD SPECTRUM
SPF 60+
60+

sun + environment
oxybenzone free

water resistant (80 minutes)
1.7 FL OZ (50 mL)